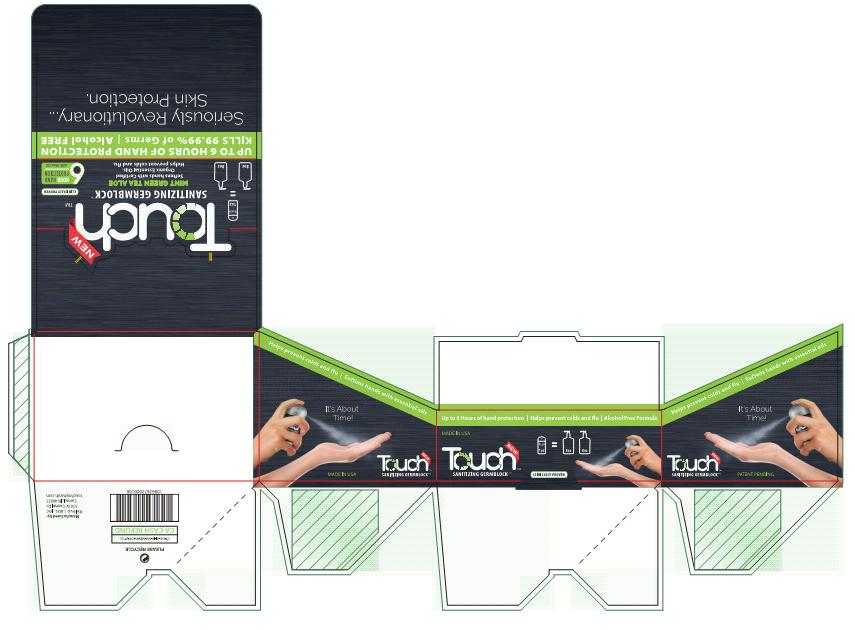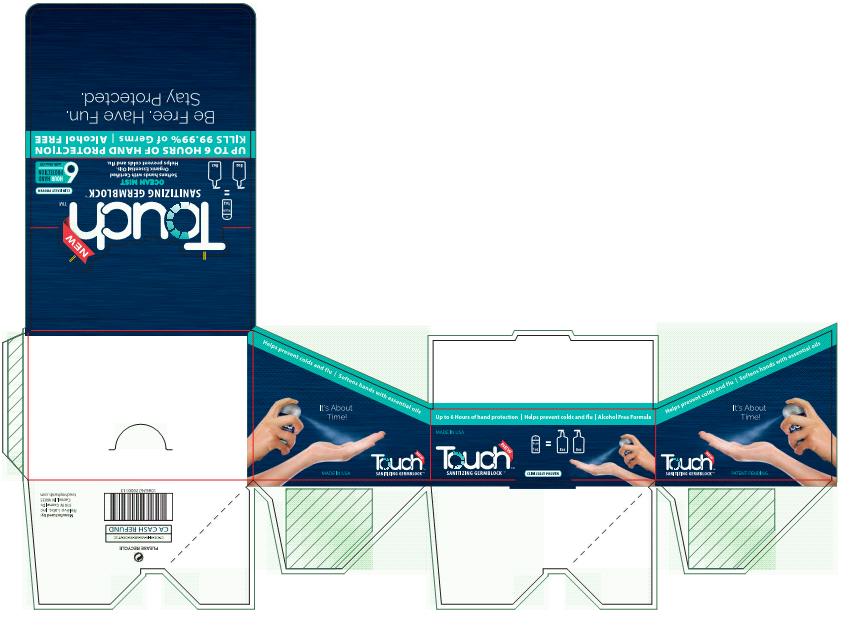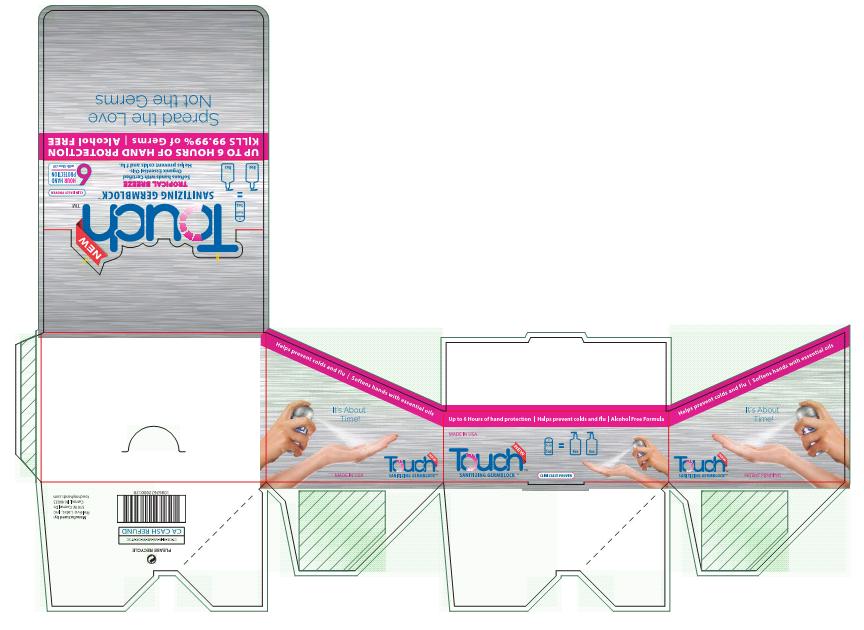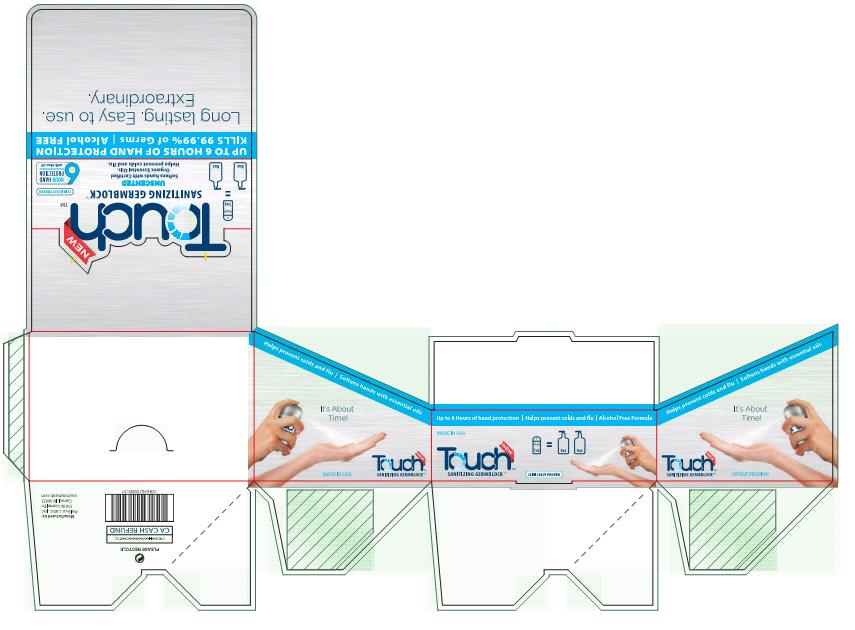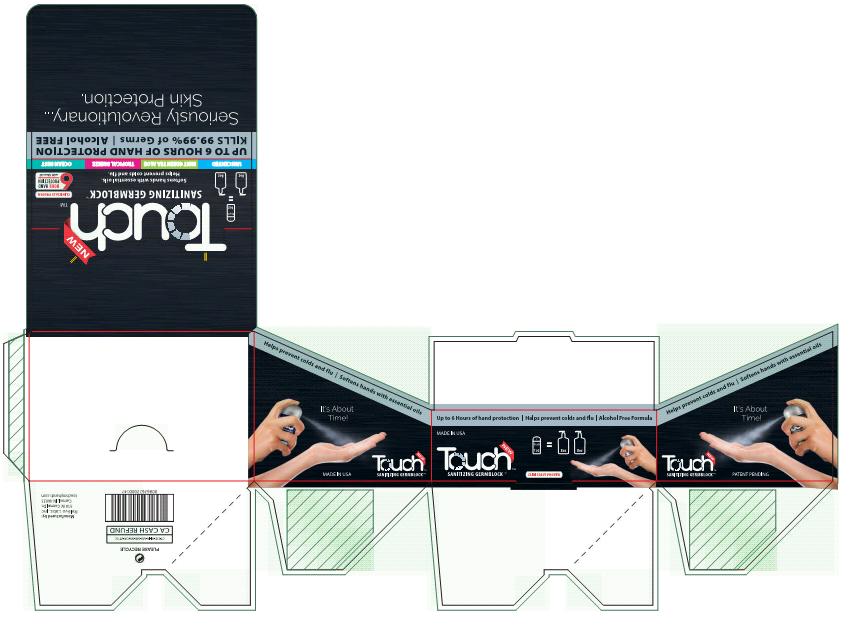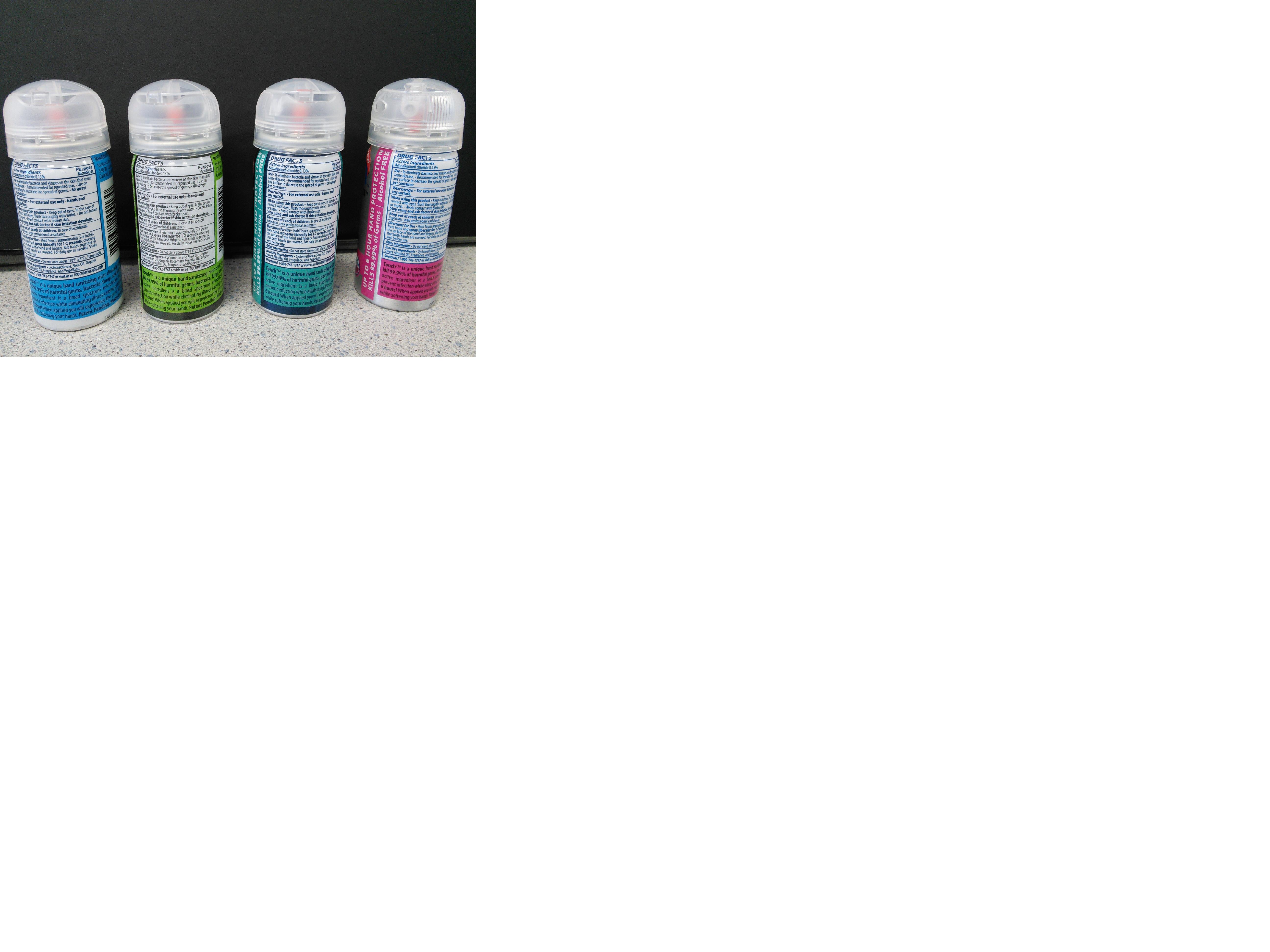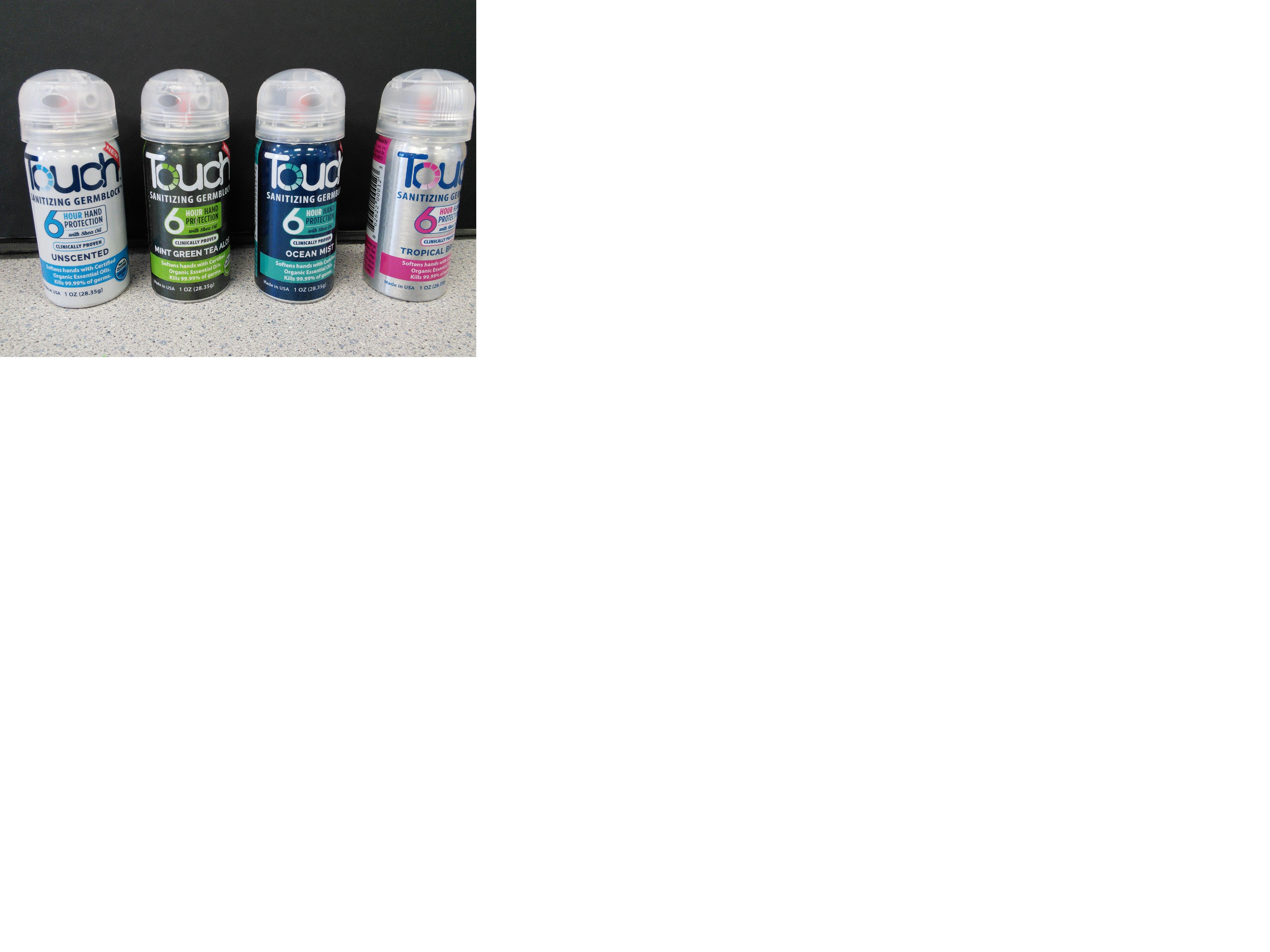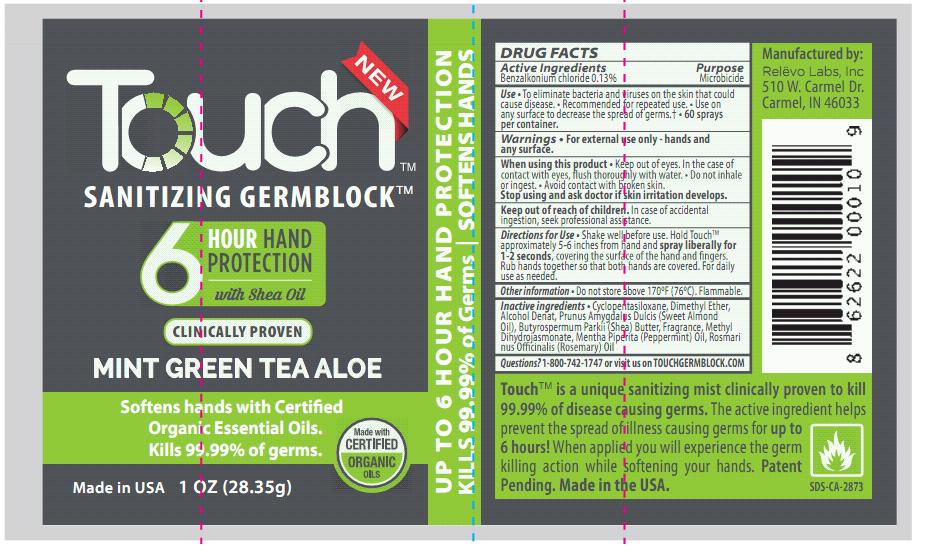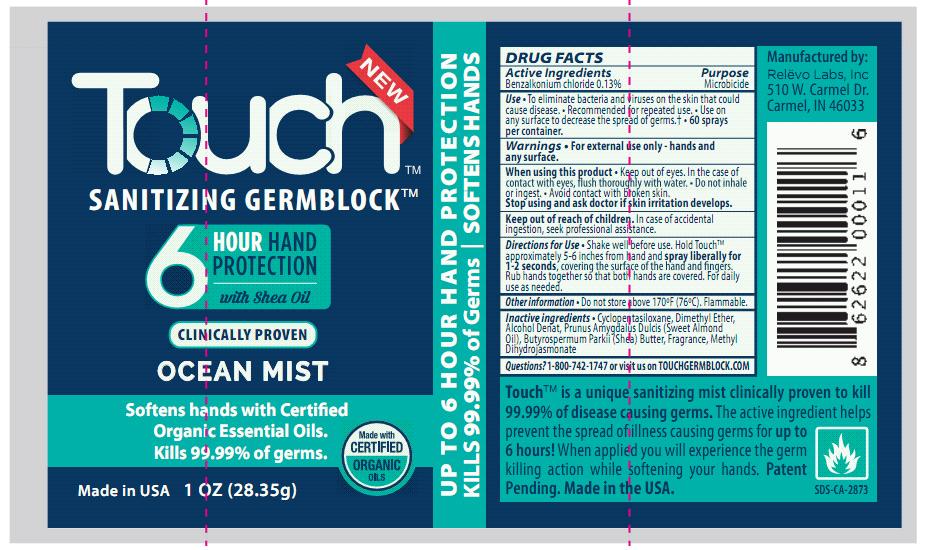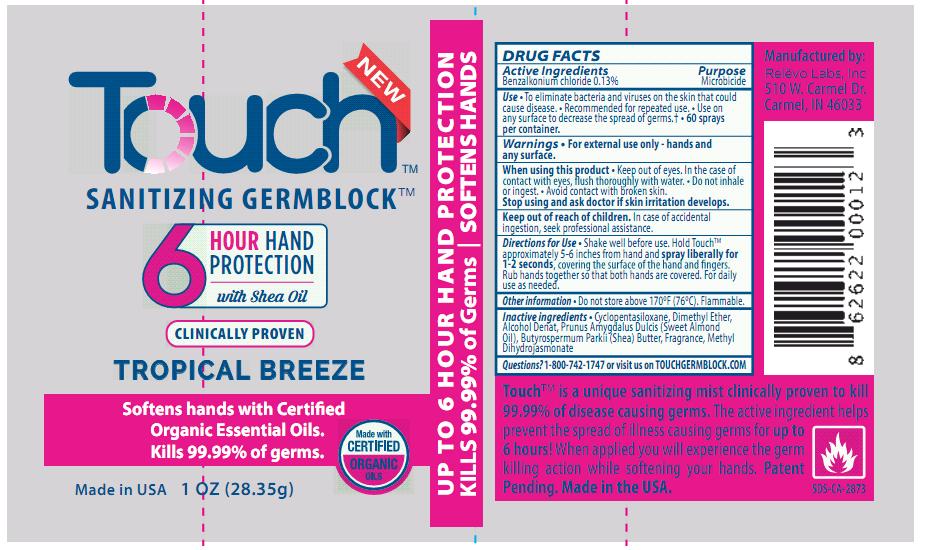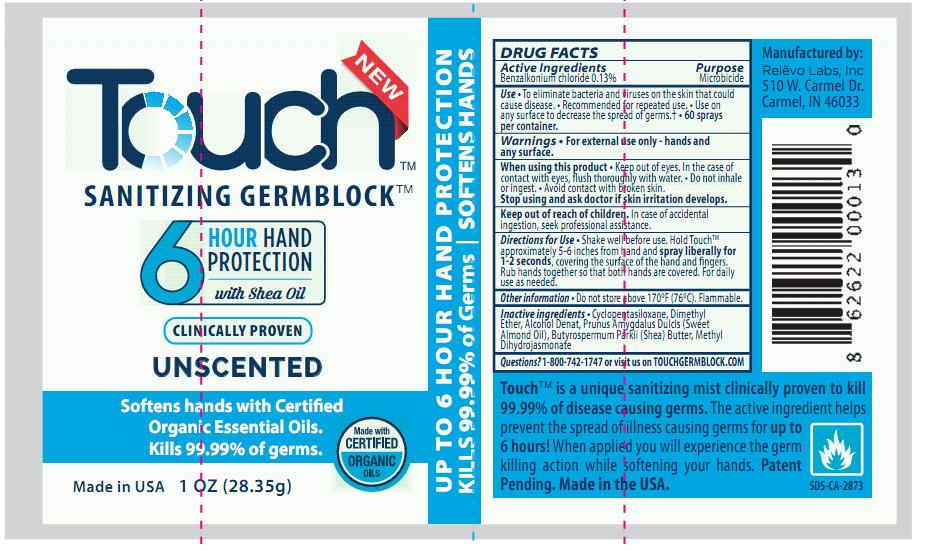 DRUG LABEL: TOUCH Sanitizing Germ Block, Unscented, 1oz (28.35g)
NDC: 69744-0201 | Form: AEROSOL, SPRAY
Manufacturer: Relevo, Inc.
Category: otc | Type: HUMAN OTC DRUG LABEL
Date: 20230516

ACTIVE INGREDIENTS: BENZALKONIUM CHLORIDE 0.13 g/100 g
INACTIVE INGREDIENTS: CYCLOMETHICONE 95 g/100 g

TOUCH Sanitizing Germ Block, 1oz (28.35g) Aerosol

Active Ingredients Purpose

Benzalkonium chloride 0.13% Microbicide

INDICATIONS AND USAGE

Use • To eliminate bacteria and viruses on the skin that could cause disease. • Recommended for repeated use. • Use on any surface to decrease the spread of germs.† • 60 sprays per container.

WARNINGS

Warnings • For external use only - hands and any surface.

When using this product • Keep out of eyes. In the case of contact with eyes, flush thoroughly with water. • Do not inhale or ingest. • Avoid contact with broken skin.

Stop using and ask doctor if skin irritation develops.

Keep out of reach of children. In case of accidental

ingestion, seek professional assistance.

INSTRUCTIONS FOR USE

Directions for Use • Shake well before use. Hold Touch approximately 5-6 inches from hand and spray liberally for 1-2 seconds covering the hands and fingers. Rub hands together so that both hands are covered. For daily use as needed.

Other information • Do not store above 170ºF (76ºC). Flammable

INACTIVE INGREDIENT

Inactive Ingredients • Cyclopentasiloxane, Dimethyl Ether, Alcohol Denat, Prunus Amygdalus Dulcis (Sweet Almond Oil), Butyrospermum Parkii (Shea) Butter, Fragrance, Methyl Dihydrojasmonate

QUESTIONS

Questions? 1-800-742-1747 or visit us on TOUCHGERMBLOCK.COM

DESCRIPTION

TOUCH is a unique hand and surface sanitizing mist clinically proven to kill 99.99% of harmful germs. The active ingredient is a broad spectrum microbicide that helps prevent infection while decreasing illness causing germs for up to 6 hours! When applied you will experience the germ killing action while softening your hands. Patent Pending. Made in the USA.

Manufactured by:
REVELO LABS, LLC
510 W. Carmel Dr. Carmel, IN 46033

DOSAGE AND ADMINISTRATION

Dosage is based on total benzalkonium chloride (the API) concentration of 0.13%. A 2 second spray yields 300 mg of product which contains 0.39 mg of API on the hands.

PURPOSE

The purpose of TOUCH Hand Sanitizer is to decrease the level of disease causing germs on the hands.

PACKAGE LABEL

TouchCartonDisplayOceanMist.jpg

TouchCartonDisplayTropicalBreeze.jpg

TouchCartonDisplayUnscented.jpg

TouchCartonDisplayVariety.jpg

TouchContainerSampleBack.jpg

TouchContainerSampleFront.jpg

TouchMintGreenTeaAloeLabel.jpg

TouchOceanMistLabel.jpg

TouchTropicalBreezeLabel.jpg

TouchUnscentedLabel.jpg